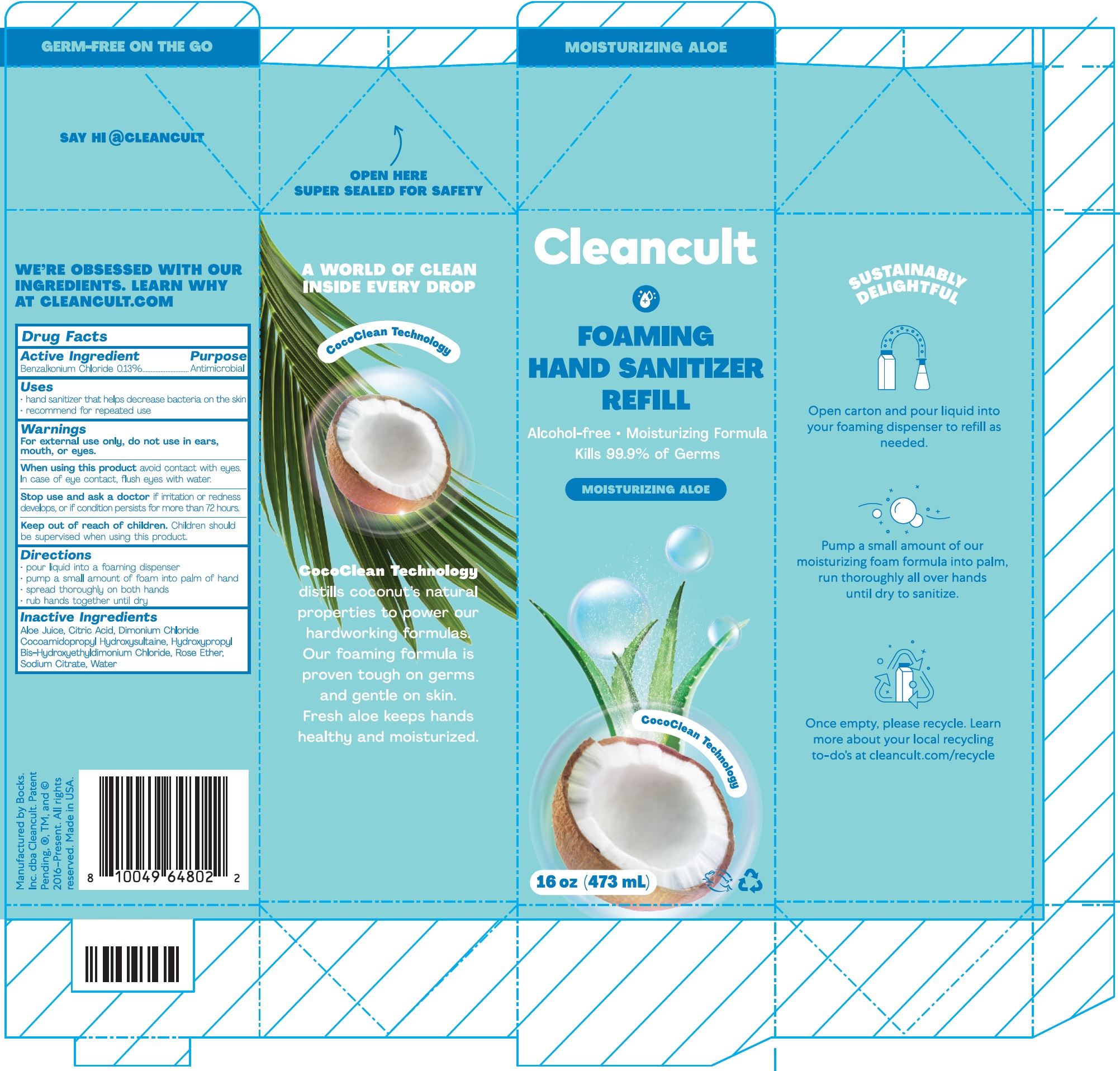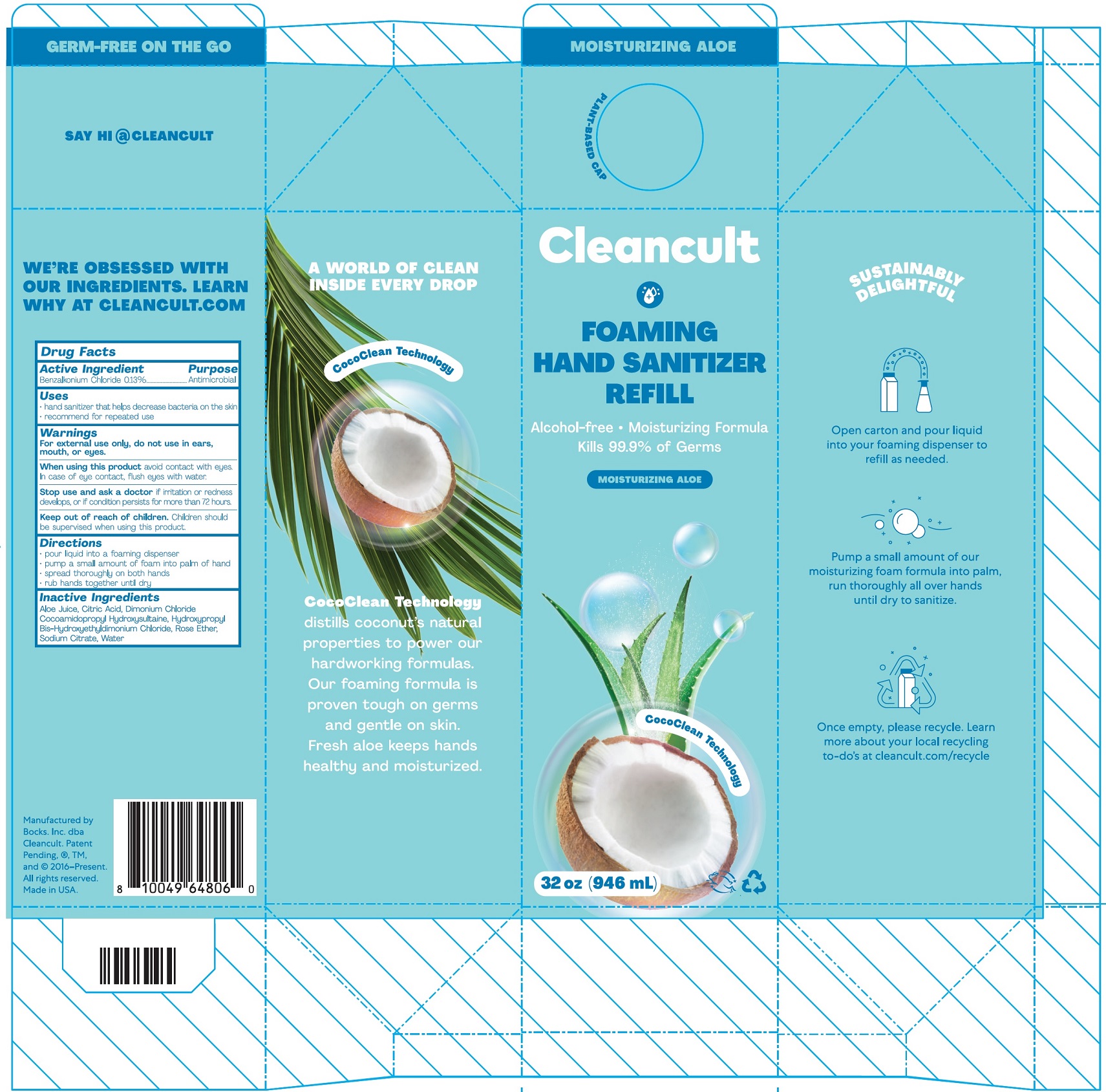 DRUG LABEL: Foaming Hand Sanitizer Refill Moisturizing Aloe
NDC: 81527-001 | Form: LIQUID
Manufacturer: Bocks Inc
Category: otc | Type: HUMAN OTC DRUG LABEL
Date: 20210208

ACTIVE INGREDIENTS: BENZALKONIUM CHLORIDE 1.3 mg/1 mL
INACTIVE INGREDIENTS: ALOE VERA LEAF; CITRIC ACID MONOHYDRATE; HYDROXYPROPYL BIS-HYDROXYETHYLDIMONIUM CHLORIDE; SODIUM CITRATE; WATER

Foaming Hand Sanitizer Refill (Moisturizing Aloe)

Active Ingredient

Benzalkonium Chloride 0.13%

Purpose

Antimicrobial

Uses

• hand sanitizer that helps decrease bacteria on the skin
• recommend for repeated use

Warnings

For external use only, do not use in ears, mouth, or eyes.

When using this product

avoid contact with eyes. In case of eye contact, flush eyes with water.

Stop use and ask a doctor

if irritation or redness develops, or if condition persists for more than 72 hours.

Keep out of reach of children

Children should be supervised when using this product.

Directions

• pour liquid into a foaming dispenser
• pump a small amount of foam into palm of hand
• spread thoroughly on both hands
• rub hands together until dry

Inactive Ingredients

Aloe Juice, Citric Acid, Dimonium Chloride Cocoamidopropyl Hydroxyethyldimonium Chloride, Hydroxypropyl Bis-Hydroxyethyldimonium Chloride,Rose Ether, Sodium Citrate, Water